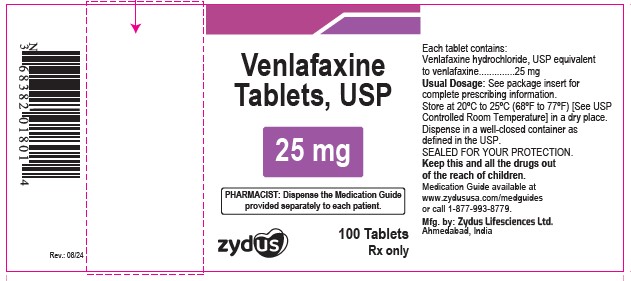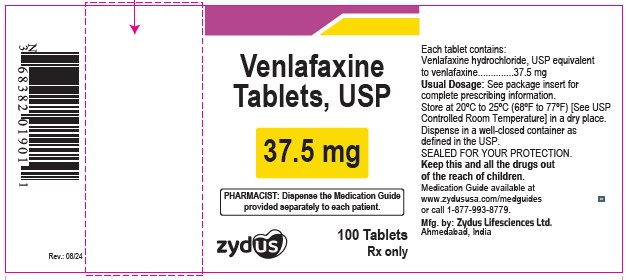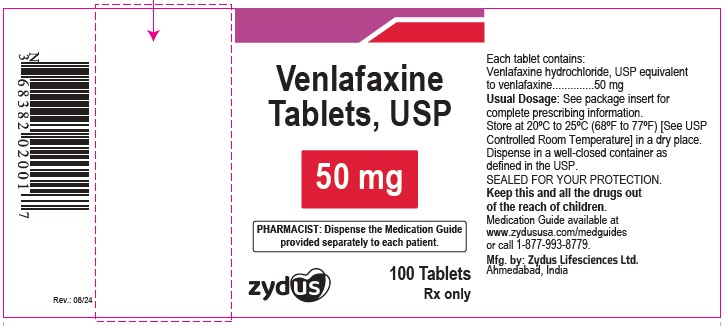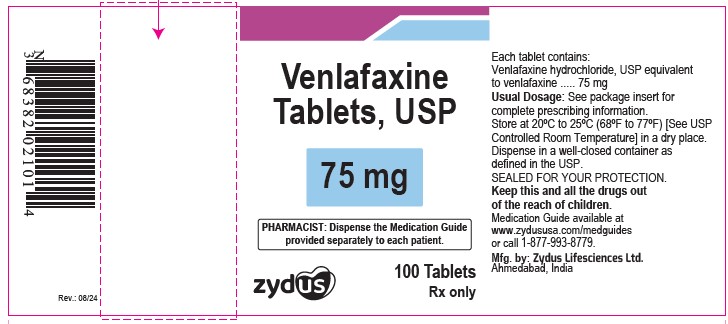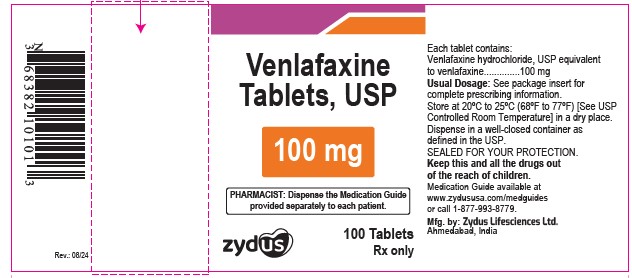 DRUG LABEL: Venlafaxine Hydrochloride
NDC: 65841-671 | Form: TABLET
Manufacturer: Zydus Lifesciences Limited
Category: prescription | Type: HUMAN PRESCRIPTION DRUG LABEL
Date: 20240814

ACTIVE INGREDIENTS: VENLAFAXINE HYDROCHLORIDE 25 mg/1 1
INACTIVE INGREDIENTS: FERRIC OXIDE YELLOW; LACTOSE MONOHYDRATE; MAGNESIUM STEARATE; SODIUM STARCH GLYCOLATE TYPE A POTATO; FERRIC OXIDE RED; CELLULOSE, MICROCRYSTALLINE

Venlafaxine Hydrochloride Tablets

PACKAGE LABEL.PRINCIPAL DISPLAY PANEL

NDC 65841-671-01 in bottle of 100 Tablets

Venlafaxine Hydrochloride Tablets, 25 mg

Rx only

100 TABLETS

NDC 65841-672-01 in bottle of 100 Tablets

Venlafaxine Hydrochloride Tablets, 37.5 mg

Rx only

100 TABLETS

NDC 65841-673-01 in bottle of 100 Tablets

Venlafaxine Hydrochloride Tablets, 50 mg

Rx only

100 TABLETS

NDC 65841-674-01 in bottle of 100 Tablets

Venlafaxine Hydrochloride Tablets, 75 mg

Rx only

100 TABLETS

NDC 65841-675-01 in bottle of 100 Tablets

Venlafaxine Hydrochloride Tablets, 100 mg

Rx only

100 TABLETS